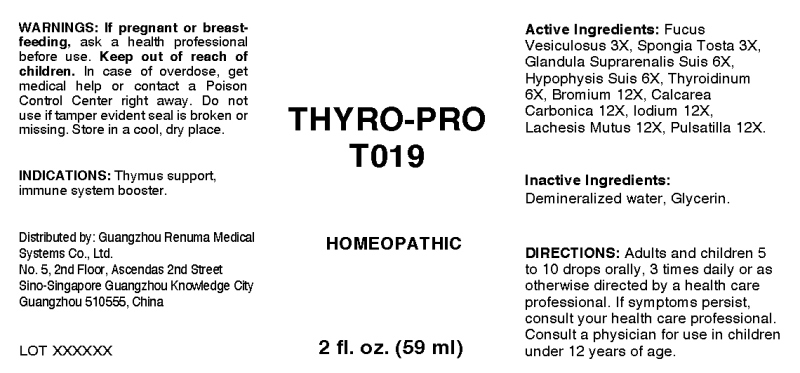 DRUG LABEL: Thyro-Pro
NDC: 71742-0013 | Form: LIQUID
Manufacturer: Guangzhou Renuma Medical Systems Co., Ltd
Category: homeopathic | Type: HUMAN OTC DRUG LABEL
Date: 20171026

ACTIVE INGREDIENTS: FUCUS VESICULOSUS 3 [hp_X]/1 mL; SPONGIA OFFICINALIS SKELETON, ROASTED 3 [hp_X]/1 mL; SUS SCROFA ADRENAL GLAND 6 [hp_X]/1 mL; SUS SCROFA PITUITARY GLAND 6 [hp_X]/1 mL; SUS SCROFA THYROID 6 [hp_X]/1 mL; BROMINE 12 [hp_X]/1 mL; OYSTER SHELL CALCIUM CARBONATE, CRUDE 12 [hp_X]/1 mL; IODINE 12 [hp_X]/1 mL; LACHESIS MUTA VENOM 12 [hp_X]/1 mL; PULSATILLA VULGARIS 12 [hp_X]/1 mL
INACTIVE INGREDIENTS: WATER; GLYCERIN

Drug Facts:

ACTIVE INGREDIENTS:

Fucus Vesiculosus 3X, Spongia Tosta 3X, Glandula Suprarenalis (Suis) 6X, Hypophysis Suis 6X, Bromium 12X, Calcarea Carbonica 12X, Iodium 12X, Lachesis Mutus 12X, Pulsatilla 12X.

INDICATIONS:

Thymus support, immune system booster.

WARNINGS:

If pregnant or breast-feeding, ask a health care professional before use.
Keep out of reach of children. In case of overdose, get medical help or contact a Poison Control Center right away.
Do not use if tamper evident seal is broken or missing.
Store in cool, dry place.

Keep out of reach of children. In case of overdose, get medical help or contact a Poison Control Center right away.

DIRECTIONS:

Adults and children 5 to 10 drops orally, 3 times daily or as otherwise directed by a health care professional. If symptoms persist, consult your health care professional. Consult a physician for use in children under 12 years of age.

INDICATIONS:

Thymus support, immune system booster.

INACTIVE INGREDIENTS:

Demineralized water, Glycerin

QUESTIONS:

Distributed by:
Guangzhou Renuma Medical
Systems Co., Ltd.
No. 5, 2nd Floor, Ascendas 2nd Street
Sino-Singapore Guangzhou Knowledge City
Guangzhou 510555, China

PACKAGE LABEL DISPLAY:

THYRO-PRO
T019
HOMEOPATHIC
2 fl. oz. (59 ml)